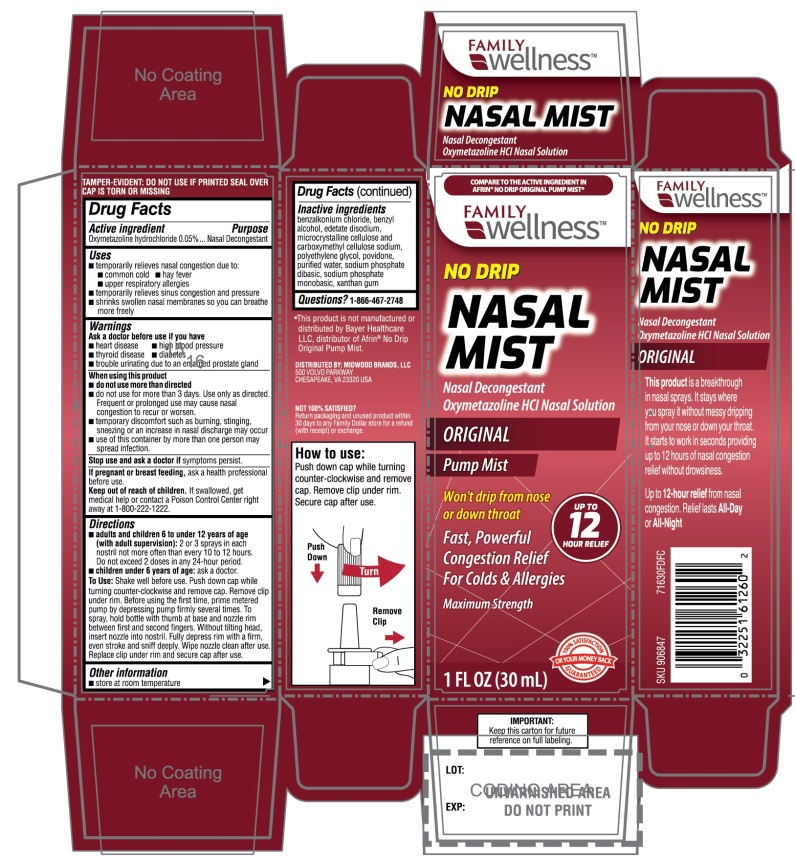 DRUG LABEL: NO DRIP

NDC: 55319-716 | Form: SPRAY
Manufacturer: FAMILY DOLLAR SERVICES INC
Category: otc | Type: HUMAN OTC DRUG LABEL
Date: 20250925

ACTIVE INGREDIENTS: OXYMETAZOLINE HYDROCHLORIDE 0.05 g/100 mL
INACTIVE INGREDIENTS: BENZALKONIUM CHLORIDE; BENZYL ALCOHOL; EDETATE DISODIUM; MICROCRYSTALLINE CELLULOSE; CARBOXYMETHYLCELLULOSE SODIUM, UNSPECIFIED; POLYETHYLENE GLYCOL, UNSPECIFIED; POVIDONE, UNSPECIFIED; WATER; SODIUM PHOSPHATE, DIBASIC, UNSPECIFIED FORM; SODIUM PHOSPHATE, MONOBASIC, UNSPECIFIED FORM; XANTHAN GUM

No Drip Nasal Mist Maximum Strength Nasal Decongestant Drug Facts

Active ingredient

Oxymetazoline hydrochloride 0.05%

Purpose

Nasal Decongestant

Uses

- temporarily relieves nasal congestion due to:
- common cold
- hay fever
- upper respiratory allergies
- temporarily relieves sinus congestion and pressure
- shrinks swollen nasal membranes so you can breathe more freely

Ask a doctor before use if you have

- heart disease
- high blood pressure
- thyroid disease
- diabetes
- trouble urinating due to an enlarged prostate gland

When using this product

- do not use more than directed
- do not use for more than 3 days. Use only as directed. Frequent or prolonged use may cause nasal congestion to recur or worsen.
- temporary discomfort such as burning, stinging, sneezing or an increase in nasal discharge may occur
- use of this container by more than one person may spread infection

Stop use and ask a doctor if

symptoms persist

If pregnant or breast-feeding,

ask a health professional before use.

Keep out of reach of children.

If swallowed, get medical help or contact a Poison Control Center right away at (1-800-222-1222).

Directions

- adults and children 6 to under 12 years of age (with adult supervision):2 or 3 sprays in each nostril not more often than every 10 to 12 hours. Do not exceed 2 doses in any 24-hour period.
- children under 6 years of age:ask a doctor

To Use:Shake well before use .Push down cap while turning counter-clockwise and remove cap. Remove clip under rim. Before using the first time, prime metered pump by depressing pump firmly several times. To spray, hold bottle with thumb at base and nozzle between first and second fingers. Without tilting head, insert nozzle into nostril. Fully depress rim with a firm, even stroke and sniff deeply. Wipe nozzle clean after use. Replace clip under rim and secure cap after use.

Other information

- store at room temperature

How to use:

Push down cap while turning counter-clockwise and remove cap. Remove clip under rim. Secure cap after use.

TAMPER-EVIDENT: DO NOT USE IF PRINTED SEAL OVER CAP IS BROKEN OR MISSING

Inactive ingredients

benzalkonium chloride, benzyl alcohol, edetate disodium, microcrystalline cellulose and carboxymethylcellulose sodium, polyethylene glycol, povidone, purified water, sodium phosphate dibasic, sodium phosphate monobasic, xanthan gum.

Questions?

1-866-467-2748

Package/Label Principal Display Panel

NDC# 55319-716-30

COMPARE TO THE ACTIVE INGREDIENT IN AFRIN® NO DRIP ORIGINAL PUMP MIST*

No DRIP

NASAL MIST

Nasal Decongestant Oxymetazoline HCl Nasal Solution

ORIGINAL Pump Mist

UP TO 12 HOUR RELIEF

Won’t drip from nose or down throat

Fast, Powerful

Congestion Relief

For Colds & Allergies

Maximum Strength

1 FL OZ (30mL)

DISTRIBUTED BY:

MIDWOOD BRANDS, LLC

500 VOLVO PARKWAY

CHESAPEAKE, VA 23320 USA

NOT 100% SATISFIED?

Return packaging and unused product within 30 days to any Family Dollar store for a refund (with receipt or exchange.

IMPORTANT:Keep this carton for future reference on full labeling.

*This product is not manufactured or distributed by Bayer Healthcare LLC, distributor of Afrin®No Drip original Pump Mist.